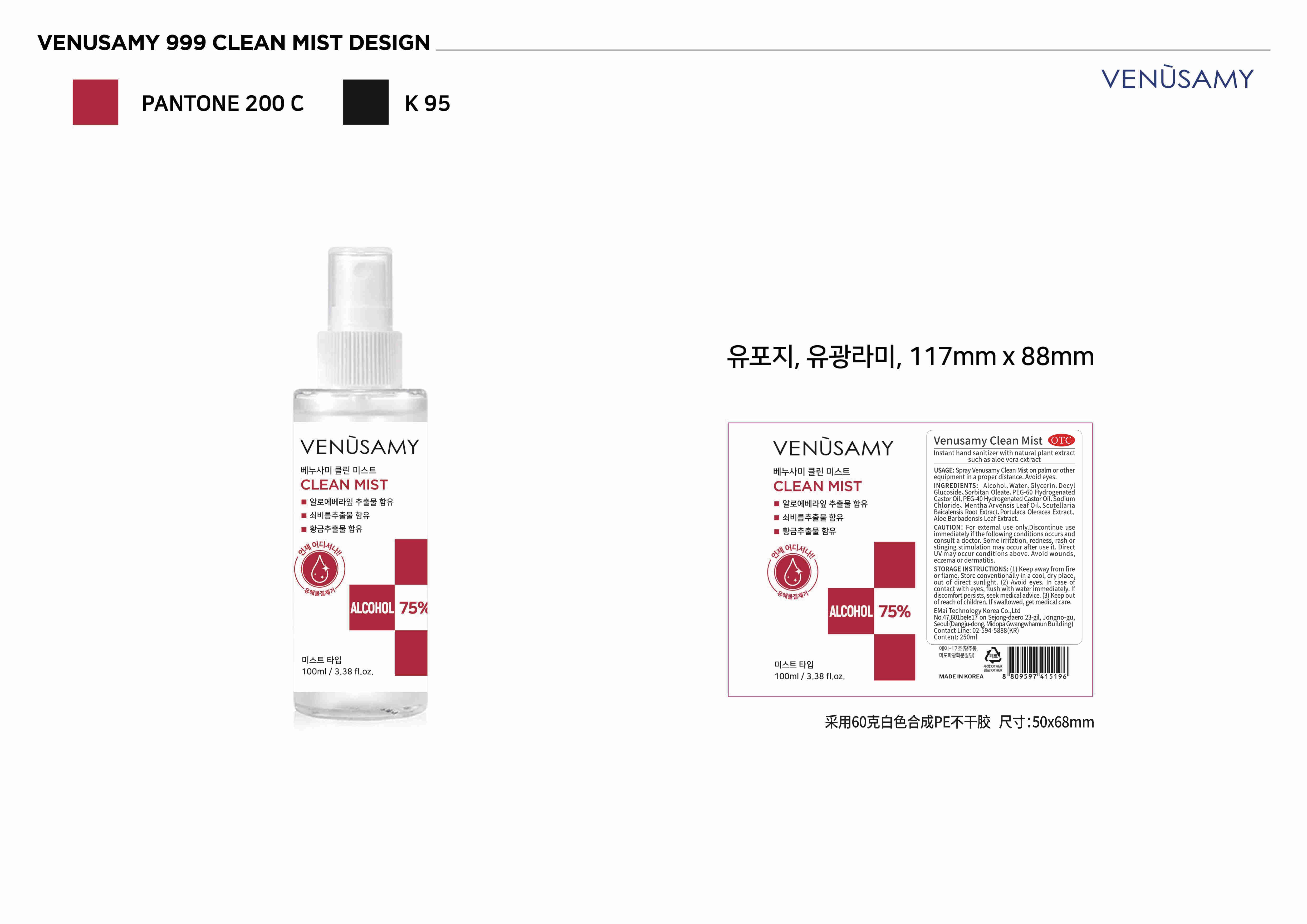 DRUG LABEL: Venusamy clean mist
NDC: 68632-003 | Form: LIQUID
Manufacturer: E-LINK GLOBAL TECH CO., LIMITED
Category: otc | Type: HUMAN OTC DRUG LABEL
Date: 20200630

ACTIVE INGREDIENTS: ALCOHOL 75 mL/100 mL
INACTIVE INGREDIENTS: SORBITAN MONOOLEATE; POLYOXYL 60 HYDROGENATED CASTOR OIL; MENTHA ARVENSIS LEAF OIL; ALOE VERA LEAF; GLYCERIN; DECYL GLUCOSIDE; WATER; POLYOXYL 40 HYDROGENATED CASTOR OIL; SODIUM CHLORIDE; SCUTELLARIA BAICALENSIS ROOT; PURSLANE

DOSAGE AND ADMINISTRATION

Store conventionally in a cool, dry place,out of direct sunlight.

INACTIVE INGREDIENT

Water

Glycerin

Decyl Glucoside

Sorbitan Oleate

PEG-60 Hydrogenated Castor Oil

PEG-40 Hydrogenated Castor Oil

Sodium Chloride

Mentha Arvensis Leaf Oil

Scutellaria Baicalensis Root Extract

Portulaca Oleracea Extract

Aloe Barbadensis Leaf Extract

INDICATIONS AND USAGE

Spray Venusamy Clean Mist on palm or other equipment in a proper distance. Avoid eyes.

ACTIVE INGREDIENT

Alcohol

keep out of reach of children

PURPOSE

Disinfection
Sterilization

WARNINGS

For external use only. Discontinue use immediately if the following conditions occurs and consult a doctor. Some irritation, redness, rash or stinging stimulation may occur after use it. Direct UV may occur conditions above. Avoid wounds, eczema or dermatitis.